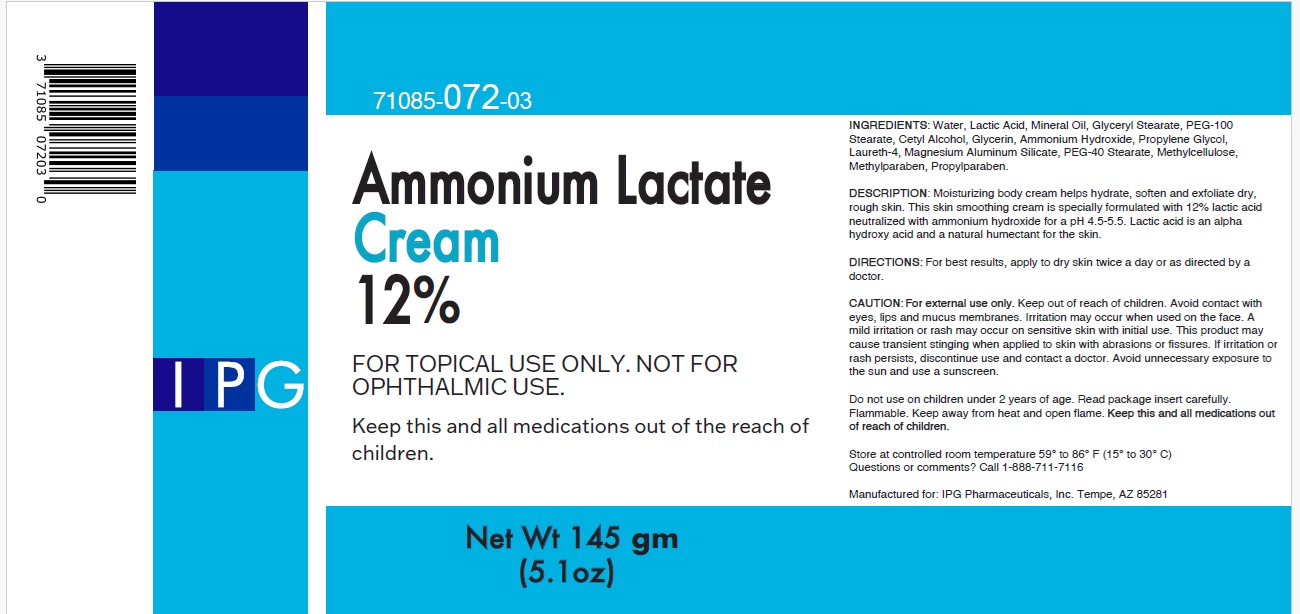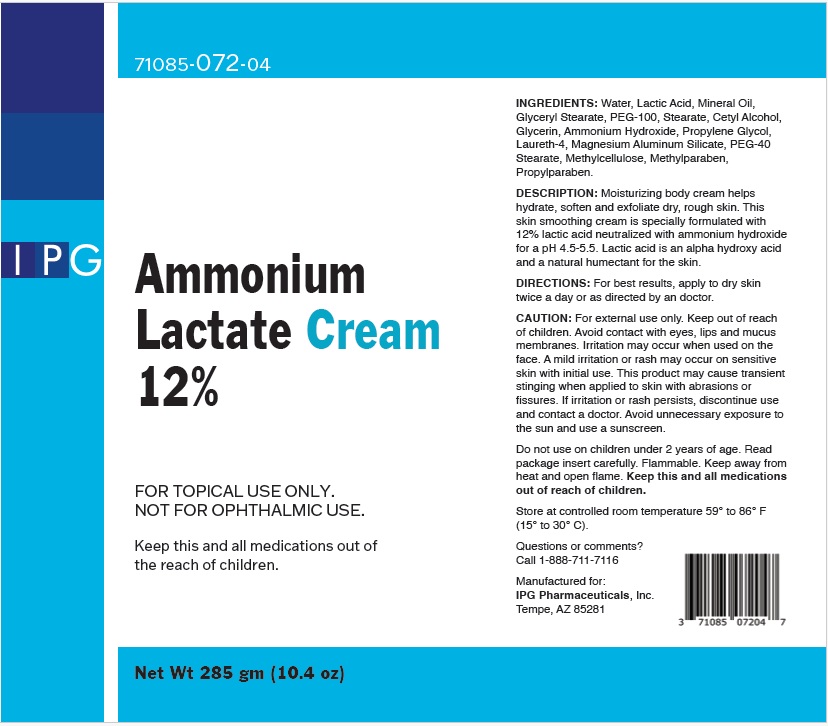 DRUG LABEL: Ammonium Lactate 12% Cream
NDC: 00371085072047
Manufacturer: IPG PHARMACEUTICALS INC
Category: other | Type: COSMETIC
Date: 20250221

Description: Moisturizing body cream helps hydrate, soften and exfoliate dry, rough skin. This skin smoothing cream is specially formulated with
12% lactic acid neutralized with ammonium hydroxide for a pH 4.5-5.5. Lactic acid is an alpha hydroxy acid and a natural humectant for the skin.

Directions: For best results, apply to dry skin twice a day or as directed by an doctor.

Ingredients: Water, Lactic Acid, Mineral Oil, Glyceryl Stearate, PEG-100, Stearate, Cetyl Alcohol, Glycerin, Ammonium Hydroxide, Propylene Glycol, Laureth-4, Magnesium Aluminum Silicate, PEG-40 Stearate, Methylcellulose, Methylparaben, Propylparaben.

Other information (if applicable)

CAUTION: For external use only. Keep out of reach of children. Avoid contact with eyes, lips and mucus membranes. Irritation may occur when used on the face. A mild irritation or rash may occur on sensitive skin with initial use. This product may cause transient stinging when applied to skin with abrasions or fissures. If irritation or rash persists, discontinue use and contact a doctor. Avoid unnecessary exposure to the sun and use a sunscreen.

Do not use on children under 2 years of age. Read package insert carefully. Flammable. Keep away from heat and open flame.

Keep this and all medications out of reach of children.

Store at controlled room temperature 59° to 86° F
(15° to 30° C).

Questions or comments?
Call 1-888-711-7116

Manufactured for:
IPG Pharmaceuticals, Inc.
Tempe, AZ 85281